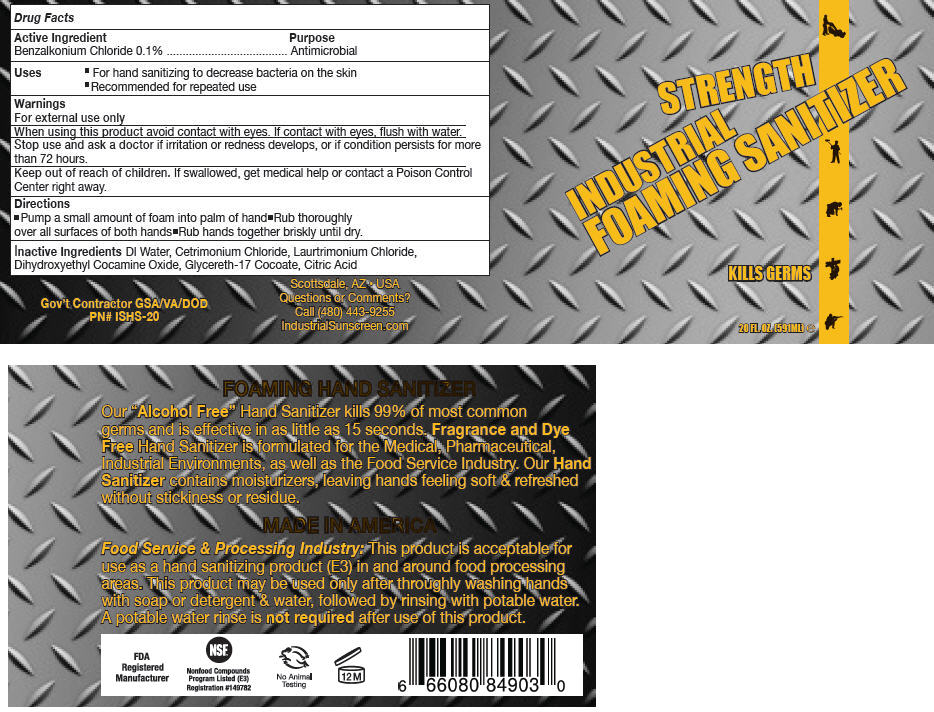 DRUG LABEL: Industrial Foaming Hand Sanitizer
NDC: 59555-402 | Form: AEROSOL, FOAM
Manufacturer: R & R Lotion, Inc
Category: otc | Type: HUMAN OTC DRUG LABEL
Date: 20151204

ACTIVE INGREDIENTS: Benzalkonium Chloride 1 mg/1 mL
INACTIVE INGREDIENTS: Water; Cetrimonium Chloride; Laurtrimonium Chloride; Dihydroxyethyl Cocamine Oxide; Glycereth-17 Cocoate; Citric Acid Monohydrate

Industrial Foaming Hand Sanitizer

Drug Facts

Active Ingredient

Benzalkonium Chloride 0.1%

Purpose

Antimicrobial

Uses

- For hand sanitizing to decrease bacteria on the skin
- Recommended for repeated use

Warnings

For external use only

When using this product avoid contact with eyes. If contact with eyes, flush with water.

Stop use and ask a doctor if irritation or redness develops, or if condition persists for more than 72 hours.

Keep out of reach of children. If swallowed, get medical help or contact a Poison Control Center right away.

Directions

- Pump a small amount of foam into palm of hand
- Rub thoroughly over all surfaces of both hands
- Rub hands together briskly until dry.

Inactive Ingredients

DI Water, Cetrimonium Chloride, Laurtrimonium Chloride, Dihydroxyethyl Cocamine Oxide, Glycereth-17 Cocoate, Citric Acid

Questions or Comments

Call (480) 443-9255

PRINCIPAL DISPLAY PANEL - 591 ML Bottle Label

STRENGTH

INDUSTRIAL
FOAMING SANITIZER

KILLS GERMS

20 FL. OZ. (591ML) e